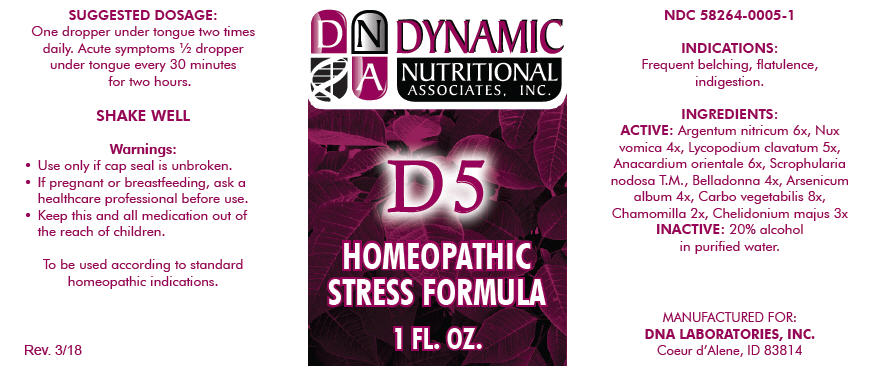 DRUG LABEL: D-5
NDC: 58264-0005 | Form: SOLUTION
Manufacturer: DNA Labs, Inc.
Category: homeopathic | Type: HUMAN OTC DRUG LABEL
Date: 20250113

ACTIVE INGREDIENTS: SILVER NITRATE 6 [hp_X]/1 mL; STRYCHNOS NUX-VOMICA SEED 4 [hp_X]/1 mL; LYCOPODIUM CLAVATUM SPORE 5 [hp_X]/1 mL; SEMECARPUS ANACARDIUM JUICE 6 [hp_X]/1 mL; SCROPHULARIA NODOSA 1 [hp_X]/1 mL; ATROPA BELLADONNA 4 [hp_X]/1 mL; ARSENIC TRIOXIDE 4 [hp_X]/1 mL; ACTIVATED CHARCOAL 8 [hp_X]/1 mL; MATRICARIA CHAMOMILLA 2 [hp_X]/1 mL; CHELIDONIUM MAJUS 3 [hp_X]/1 mL
INACTIVE INGREDIENTS: ALCOHOL; WATER

D-5

NDC 58264-0005-1

INDICATIONS

PURPOSE

Frequent belching, flatulence, indigestion.

INGREDIENTS

ACTIVE

Argentum nitricum 6x, Nux vomica 4x, Lycopodium clavatum 5x, Anacardium orientale 6x, Scrophularia nodosa T.M., Belladonna 4x, Arsenicum album 4x, Carbo vegetabilis 8x, Chamomilla 2x, Chelidonium majus 3x

INACTIVE

20% alcohol in purified water.

SUGGESTED DOSAGE

One dropper under tongue two times daily. Acute symptoms ½ dropper under tongue every 30 minutes for two hours.

STORAGE AND HANDLING

SHAKE WELL

Warnings

- Use only if cap seal is unbroken.

PREGNANCY OR BREAST FEEDING

- If pregnant or breastfeeding, ask a healthcare professional before use.

KEEP OUT OF REACH OF CHILDREN

- Keep this and all medication out of the reach of children.

To be used according to standard homeopathic indications.

PRINCIPAL DISPLAY PANEL - 1 FL. OZ. Bottle Label

DYNAMIC
NUTRITIONAL
ASSOCIATES, INC.

D 5

HOMEOPATHIC
STRESS FORMULA

1 FL. OZ.